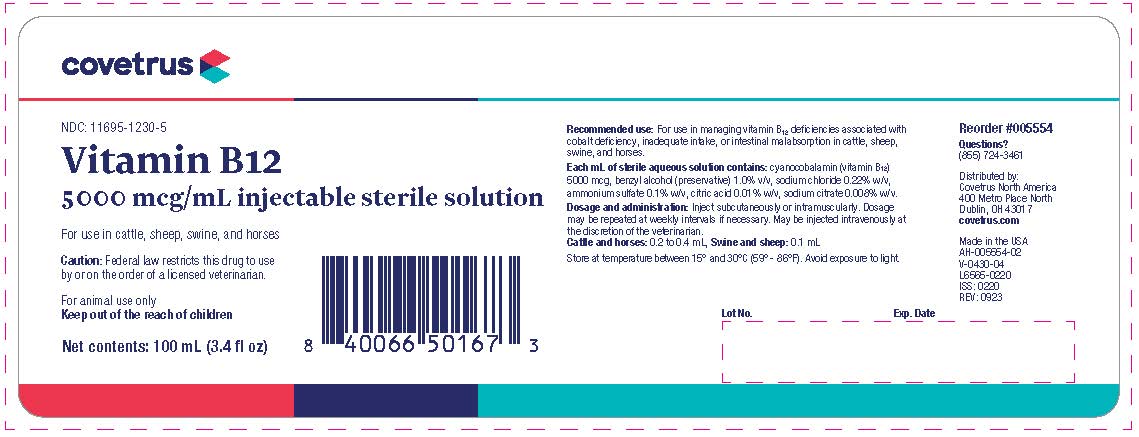 DRUG LABEL: Vitamin B12
NDC: 11695-1230 | Form: INJECTION
Manufacturer: Covetrus North America
Category: animal | Type: PRESCRIPTION ANIMAL DRUG LABEL
Date: 20231219

ACTIVE INGREDIENTS: CYANOCOBALAMIN 5 mg/1 mL
INACTIVE INGREDIENTS: BENZYL ALCOHOL; WATER; SODIUM CHLORIDE; AMMONIUM SULFATE; ANHYDROUS CITRIC ACID; SODIUM CITRATE

Vitamin B12 Injection
5000 mcg/mL Injectable Sterile Solution

Recommended use:

For use in managing Vitamin B12 deficiencies associated with cobalt deficiency, inadequate intake, or intestinal malabsorption in
cattle, sheep, swine, and horses.

Each mL of sterile aqueous solution contains:

Cyanocobalamin (Vitamin B12) 5000 mcg, Benzyl Alcohol (preservative) 1.0% v/v, Sodium Chloride 0.22% w/v, Ammonium
Sulfate 0.1% w/v, Citric Acid 0.01% w/v, Sodium Citrate 0.008% w/v.

Dosage and Administration:

Inject subcutaneously or intramuscularly. Dosage may be repeated at weekly intervals if
necessary. May be injected intravenously at the discretion of the veterinarian.
Cattle and Horses: 0.2 to 0.4 mL, Swine and Sheep: 0.1 mL

STORAGE AND HANDLING

Store at temperature between 15° and 30°C (59° - 86°F). Avoid exposure to light.

Reorder #005554

Questions?
(855) 724-3461

Distributed by:Covetrus North America
400 Metro Place North
Dublin, OH 43017
covetrus.com

Made in USA